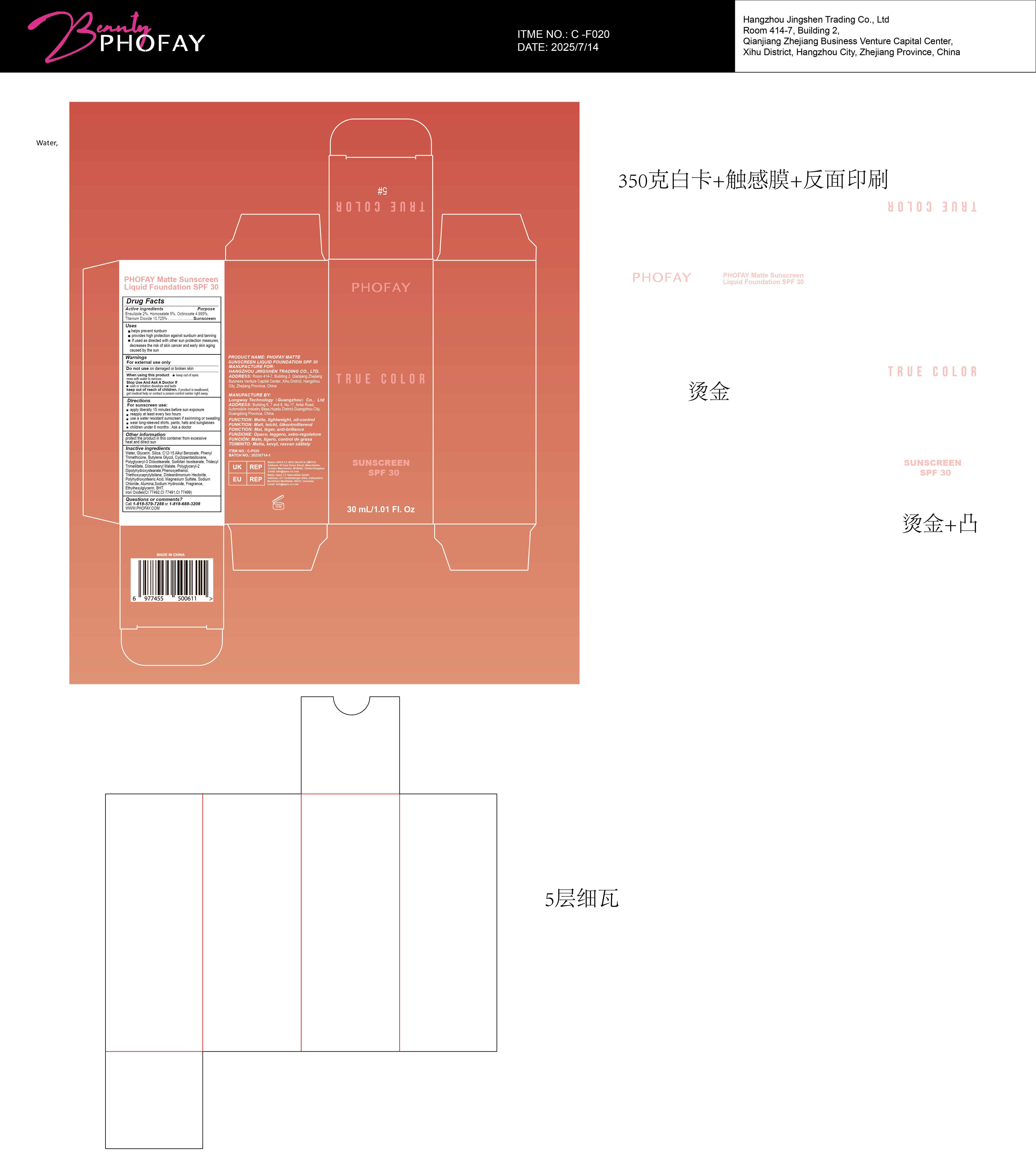 DRUG LABEL: PHOFAY Matte Sunscreen Liquid Foundation SPF 30 5
NDC: 87080-105 | Form: LOTION
Manufacturer: Hangzhou Jingshen Trading Co., Ltd.
Category: otc | Type: HUMAN OTC DRUG LABEL
Date: 20250906

ACTIVE INGREDIENTS: TITANIUM DIOXIDE 0.10725 g/1 g; ENSULIZOLE 0.02 g/1 g; HOMOSALATE 0.05 g/1 g; OCTINOXATE 0.04995 g/1 g
INACTIVE INGREDIENTS: SODIUM HYDROXIDE; FRAGRANCE LEMON ORC2001060; BUTYLENE GLYCOL; BHT; POLYHYDROXYSTEARIC ACID (2300 MW); MAGNESIUM SULFATE; SILICON DIOXIDE; TRIDECYL TRIMELLITATE; ETHYLHEXYLGLYCERIN; SORBITAN ISOSTEARATE; WATER; CYCLOPENTASILOXANE; CI 77492; C12-15 ALKYL BENZOATE; ALUMINA; PHENYL TRIMETHICONE; POLYGLYCERYL-3 DIISOSTEARATE; DISTEARDIMONIUM HECTORITE; GLYCERIN; DIISOSTEARYL MALATE; POLYGLYCERYL-2 DIPOLYHYDROXYSTEARATE; SODIUM CHLORIDE; CI 77499; PHENOXYETHANOL; CI 77491; TRIETHOXYCAPRYLYLSILANE

ACTIVE INGREDIENT

Ensulizole 2%,Homosalate 5%,Octinoxate 4.995%,Titanium Dioxide 10.725%

KEEP OUT OF REACH OF CHILDREN

if product is swallowed,get medical help or contact a poison control center right away.

WARNINGS

For external use only

Do not use on damaged or broken skin

When using this product keep out of eyes.

rinse with water to remove.

Stop Use And Ask A Doctor lf

rash or irritation develops and lasts

keep out of reach of children.

if product is swallowed,get medical help or contact a poison control center right away.

DOSAGE AND ADMINISTRATION

For sunscreen use:
apply liberally 15 minutes before sun exposure

reapply at least every two hours

use a water resistant sunscreen if swimming or sweating

wear long-sleeved shirts, pants, hats and sunglasses

children under 6 months :Ask a doctor

OTHER SAFETY INFORMATION

protect the product in this container from excessive

heat and direct sun

INACTIVE INGREDIENT

Water, Glycerin, Silica, C12-15 Alkyl Benzoate, Phenyl Trimethicone, Butylene Glycol, Cyclopentasiloxane, Polyglyceryl-3 Diisostearate, Sorbitan Isostearate, Tridecyl Trimellitate, Diisostearyl Malate, Polyglyceryl-2 Dipolyhydroxystearate,Phenoxyethanol, Triethoxycaprylylsilane, Disteardimonium Hectorite, Polyhydroxystearic Acid, Magnesium Sulfate, Sodium Chloride, Alumina,Sodium Hydroxide, Fragrance, Ethylhexylglycerin, BHT,Iron Oxides(CI 77492,CI 77491,CI 77499)

PURPOSE

Suncreen

INDICATIONS AND USAGE

helps prevent sunburn

provides high protection against sunburn and tanning

lf used as directed with other sun protection measures.

decreases the risk of skin cancer and early skin aging caused by the sun

QUESTIONS

Call 1-818-579-72880 or 1-818-688-3208

WWW.PHOFAY.COM